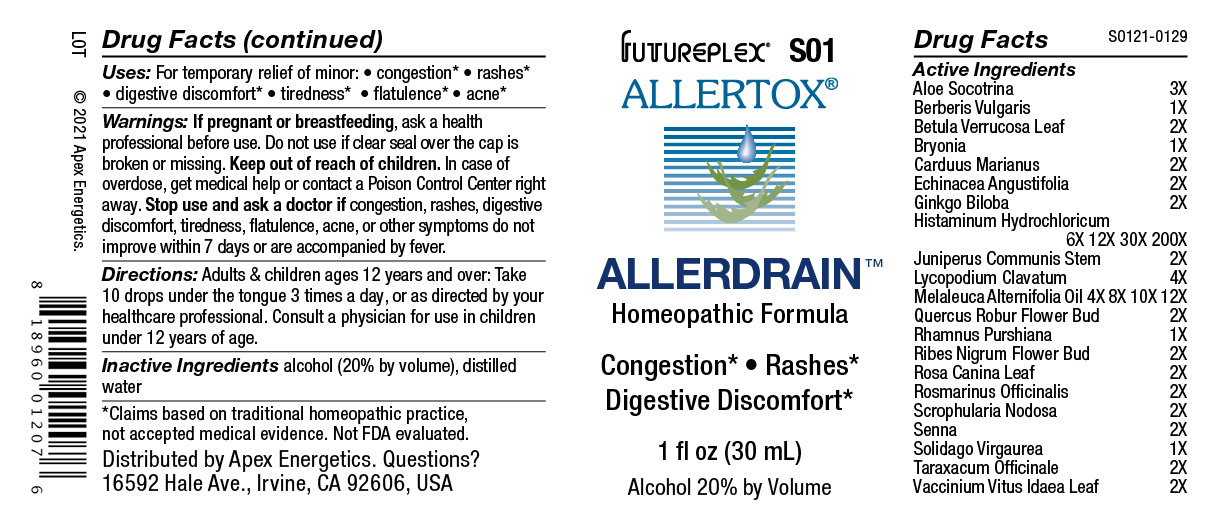 DRUG LABEL: S01
NDC: 63479-1901 | Form: SOLUTION/ DROPS
Manufacturer: Apex Energetics Inc.
Category: homeopathic | Type: HUMAN OTC DRUG LABEL
Date: 20240108

ACTIVE INGREDIENTS: LYCOPODIUM CLAVATUM SPORE 4 [hp_X]/1 mL; FRANGULA PURSHIANA BARK 1 [hp_X]/1 mL; QUERCUS ROBUR FLOWER BUD 2 [hp_X]/1 mL; RIBES NIGRUM FLOWER BUD 2 [hp_X]/1 mL; ROSA CANINA LEAF 2 [hp_X]/1 mL; SCROPHULARIA NODOSA 2 [hp_X]/1 mL; MILK THISTLE 2 [hp_X]/1 mL; GINKGO 2 [hp_X]/1 mL; HISTAMINE DIHYDROCHLORIDE 200 [hp_X]/1 mL; TEA TREE OIL 12 [hp_X]/1 mL; ROSMARINUS OFFICINALIS FLOWERING TOP 2 [hp_X]/1 mL; BERBERIS VULGARIS ROOT BARK 1 [hp_X]/1 mL; BETULA PENDULA LEAF 2 [hp_X]/1 mL; BRYONIA ALBA ROOT 1 [hp_X]/1 mL; ALOE 3 [hp_X]/1 mL; JUNIPERUS COMMUNIS STEM 2 [hp_X]/1 mL; VACCINIUM VITIS-IDAEA LEAF 2 [hp_X]/1 mL; ECHINACEA ANGUSTIFOLIA 2 [hp_X]/1 mL; TARAXACUM OFFICINALE 2 [hp_X]/1 mL; SENNA LEAF 2 [hp_X]/1 mL; SOLIDAGO VIRGAUREA FLOWERING TOP 1 [hp_X]/1 mL
INACTIVE INGREDIENTS: WATER; ALCOHOL

S01

Active Ingredients
Aloe Socotrina | 3X
Berberis Vulgaris | 1X
Betula Verrucosa Leaf | 2X
Bryonia | 1X
Carduus Marianus | 2X
Echinacea Angustifolia | 2X
Ginkgo Biloba | 2X
Histaminum Hydrochloricum | 6X 12X 30X 200X
Juniperus Communis Stem | 2X
Lycopodium Clavatum | 4X
Melaleuca Alternifolia Oil | 4X 8X 10X 12X
Quercus Robur Flower Bud | 2X
Rhamnus Purshiana | 1X
Ribes Nigrum Flower Bud | 2X
Rosa Canina Leaf | 2X
Rosmarinus Officinalis | 2X
Scrophularia Nodosa | 2X
Senna | 2X
Solidago Virgaurea | 1X
Taraxacum Officinale | 2X
Vaccinium Vitus-Idaea Leaf | 2X

INDICATIONS AND USAGE

Uses:

For temporary relief of minor:

congestion*

rashes*

digestive discomfort*

tiredness*

flatulence*

acne*

*Claims based on traditional homeopathic practice, not accepted medical evidence. Not FDA evaluated.

Warnings:

PURPOSE

If pregnant or breastfeeding, ask a health professional before use.

Do not use if clear seal over the cap is broken or missing.

Keep out of reach of children. In case of overdose, get medical help or contact a Poison Control Center right away.

Stop use and ask a doctor if congestion, rashes, digestive discomfort, tiredness, flatulence, acne, or other symptoms do not improve within 7 days or are accompanied by fever.

Directions:

Adults & children ages 12 years and over: Take 10 drops under the tongue 3 times a day, or as directed by your healthcare professional. Consult a physician for use in children under 12 years of age.

Inactive Ingredients

alcohol (20% by volume), distilled water

Distributed by Apex Energetics. Questions?

16592 Hale Ave., Irvine, CA 92606, USA

PACKAGE LABEL

FUTUREPLEX® S01

ALLERTOX®

ALLERDRAIN™

Homeopathic Formula

Congestion*

Rashes*

Digestive Discomfort*

1 fl oz (30 mL)

Alcohol 20% by Volume